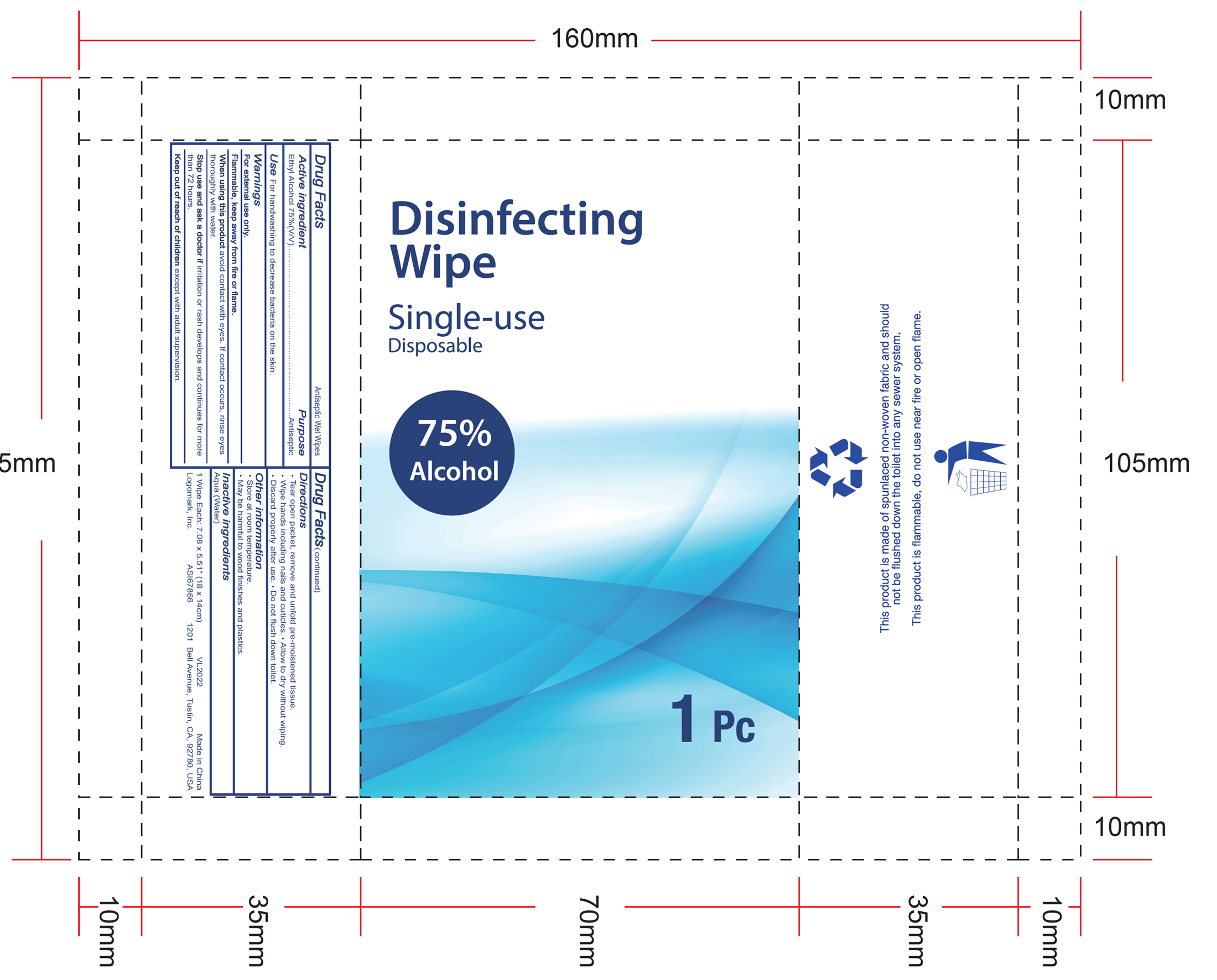 DRUG LABEL: sanitizing wipes
NDC: 76806-002 | Form: CLOTH
Manufacturer: Logomark Inc
Category: otc | Type: HUMAN OTC DRUG LABEL
Date: 20200625

ACTIVE INGREDIENTS: ALCOHOL 0.75 mL/1 g
INACTIVE INGREDIENTS: WATER

sanitizing wipes

Active Ingredient(s)

Alcohol 75%. Purpose: Antiseptic

Purpose

Antiseptic

Use

For handwashing to decrease bacteria on the skin.

Warnings

For external use only.

Flmmable, keep away from fire or flame.

When using this product

avoid contact with eyes. In contact occurs, rinse eyes thoroughly with water

Stop use and ask a doctor if irritation or rash develops and continues for more than 72 hours

Keep out of reach of children except with adult supervision.

Directions

- Tear open package, remove and unfold pre-moistened tissue.
- Wipe hands including nails and cuticles.
- Allow to dry without wiping.
- Discard property after use.
- Do not flush down toilet.

Other information

- Store at room temperature.
- May be harmful to wood finishes and plastics

Inactive ingredients

Aqua (Water)

Package Label - Principal Display Panel

1 PC NDC: 76806-002-01